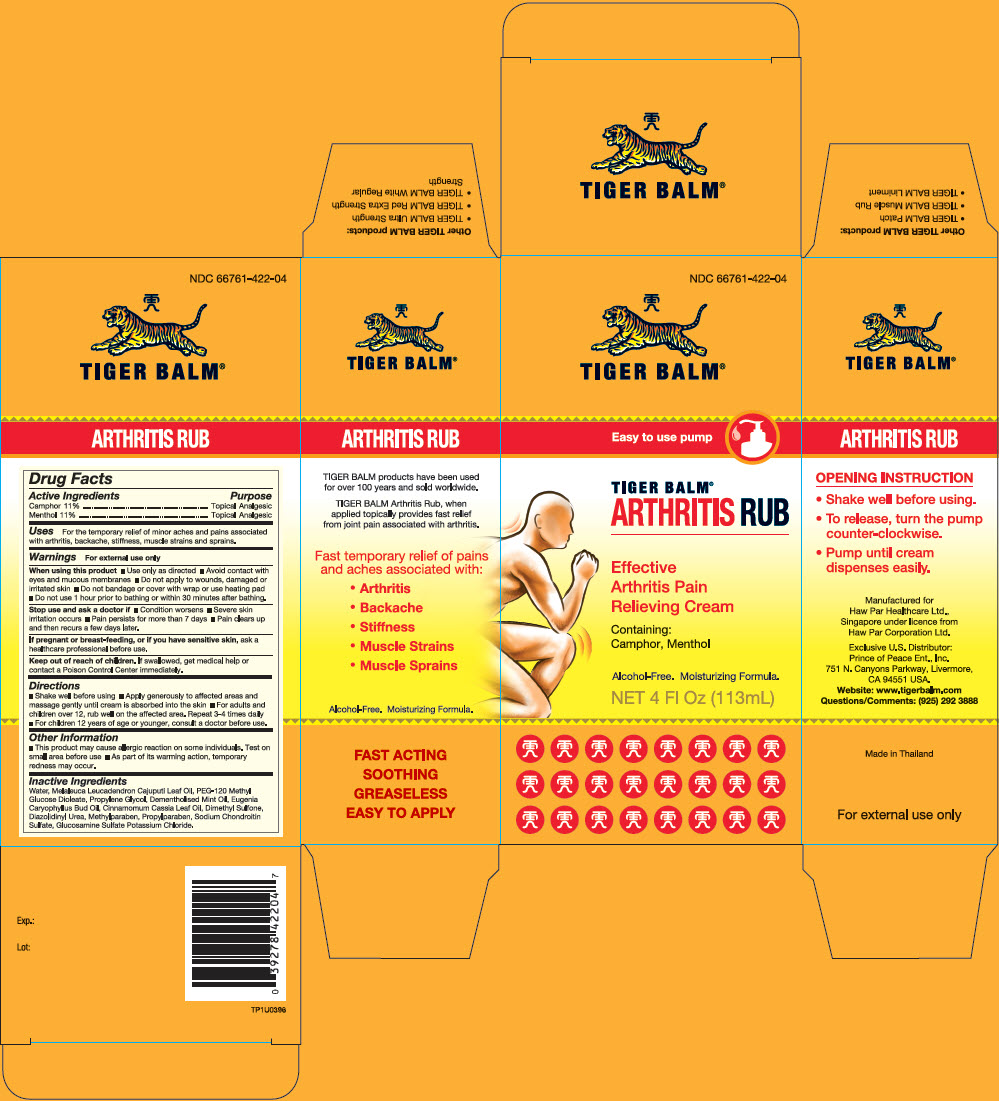 DRUG LABEL: Tiger Balm 
NDC: 66761-422 | Form: CREAM
Manufacturer: Haw Par Healthcare Ltd.
Category: otc | Type: HUMAN OTC DRUG LABEL
Date: 20240108

ACTIVE INGREDIENTS: Camphor (Synthetic) 110 mg/1 mL; Menthol, Unspecified Form 110 mg/1 mL
INACTIVE INGREDIENTS: Cajuput Oil; Cinnamon Oil; Clove Oil; Water; Diazolidinyl Urea; Glucosamine Sulfate; Methylparaben; Dimethyl Sulfone; PEG-120 Methyl Glucose Dioleate; Propylparaben; Propylene Glycol

Tiger Balm®
Arthritis Rub

Drug Facts

ACTIVE INGREDIENT

Active Ingredients | Purpose
Camphor 11% | Topical Analgesic
Menthol 11% | Topical Analgesic

Uses

For the temporary relief of minor aches and pains associated with arthritis, backache, stiffness, muscle strains and sprains.

Warnings

For external use only

When using this product

- Use only as directed
- Avoid contact with eyes and mucous membranes
- Do not apply to wounds, damaged or irritated skin
- Do not bandage or cover with wrap or use heating pad
- Do not use 1 hour prior to bathing or within 30 minutes after bathing.

Stop use and ask a doctor if

- Condition worsens
- Severe skin irritation occurs
- Pain persists for more than 7 days
- Pain clears up and then recurs a few days later.

PREGNANCY OR BREAST FEEDING

If pregnant or breast-feeding, or if you have sensitive skin, ask a healthcare professional before use.

Keep out of reach of children. If swallowed, get medical help or contact a Poison Control Center immediately.

Directions

- Shake well before using
- Apply generously to affected areas and massage gently until cream is absorbed into the skin
- For adults and children over 12, rub well on the affected area. Repeat 3-4 times daily
- For children 12 years of age or younger, consult a doctor before use.

Other Information

- This product may cause allergic reaction on some individuals. Test on small area before use
- As part of its warming action, temporary redness may occur.

Inactive Ingredients

Cajuput Oil, Chondroitin Sulfate, Cinnamon Oil, Clove Oil, Purified Water, Dementholised Mint Oil, Diazolidinyl Urea, Glucosamine Sulfate, Methyl Paraben, Methylsulfonylmethane (MSM), PEG-120 Methyl Glucose Dioleate, Propyl Paraben, Propylene Glycol.

Questions/Comments

(925) 292 3888

PRINCIPAL DISPLAY PANEL - 113 mL Bottle Carton

NDC 66761-422-04

TIGER BALM®

Easy to use pump

TIGER BALM®
ARTHRITIS RUB

Effective
Arthritis Pain
Relieving Cream

Containing:
Camphor, Menthol

Alcohol-Free. Moisturizing Formula.

NET 4 Fl Oz (113mL)